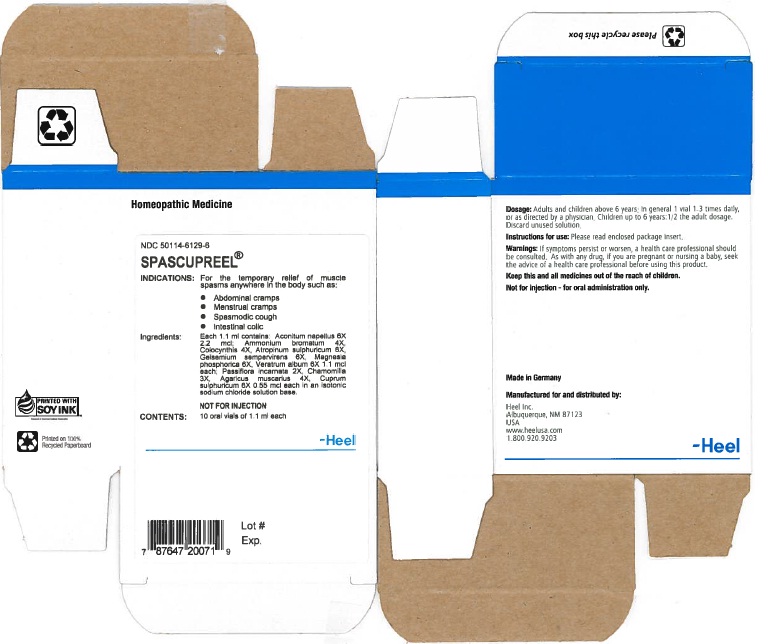 DRUG LABEL: Spascupreel
NDC: 50114-6129 | Form: SOLUTION
Manufacturer: Heel Inc
Category: homeopathic | Type: HUMAN OTC DRUG LABEL
Date: 20120509

ACTIVE INGREDIENTS: ACONITUM NAPELLUS 6 [hp_X]/1.1 mL; AMMONIUM BROMIDE 4 [hp_X]/1.1 mL; CITRULLUS COLOCYNTHIS FRUIT PULP 4 [hp_X]/1.1 mL; ATROPINE SULFATE 6 [hp_X]/1.1 mL; GELSEMIUM SEMPERVIRENS ROOT 6 [hp_X]/1.1 mL; MAGNESIUM PHOSPHATE, DIBASIC TRIHYDRATE 6 [hp_X]/1.1 mL; VERATRUM ALBUM ROOT 6 [hp_X]/1.1 mL; PASSIFLORA INCARNATA FLOWERING TOP 2 [hp_X]/1.1 mL; MATRICARIA RECUTITA 3 [hp_X]/1.1 mL; AMANITA MUSCARIA VAR. MUSCARIA FRUITING BODY 4 [hp_X]/1.1 mL; CUPRIC SULFATE 6 [hp_X]/1.1 mL
INACTIVE INGREDIENTS: SODIUM CHLORIDE

Spascupreel 1.1ml Oral Vial

ACTIVE INGREDIENTS

Active ingredients: Each 1.1 ml contains: Aconitum napellus 6X 2.2 mcl; Ammonium bromatum 4X, Colocynthis 4X, Atropinum sulphuricum 6X, Gelsemium sempervirens 6X, Magnesia phosphorica 6X, Veratrum album 6X 1.1 mcl each; Passiflora incarnata 2X, Chamomilla 3X, Agaricus muscarius 4X, Cuprum sulphuricum 6X 0.55 mcl each.

PURPOSE

Abdominal cramps, Menstrual cramps, Spasmodic cough, Intestinal colic

KEEP OUT OF REACH OF CHILDREN

Keep this and all medicines out of the reach of children.

INDICATIONS AND USAGE

Indications: For the temporary relief of muscle spasms anywhere in the body such as:

- Abdominal cramps
- Menstrual cramps
- Spasmodic cough
- Intestinal colic

WARNINGS

Warnings: If symptoms persist or worsen, a health care professional should be consulted. As with any drug, if you are pregnant or nursing a baby, seek the advise of a health care professional before using this product.

DOSAGE AND ADMINISTRATION

Dosasge: Adults and children above 6 years: In general 1 vial 1 - 3 times daily, or as directed by a physician. Children up to 6 years: 1/2 the adult dosage. Discard unused solution.

INACTIVE INGREDIENTS

Inactive ingredients: Isotonic sodium chloride solution